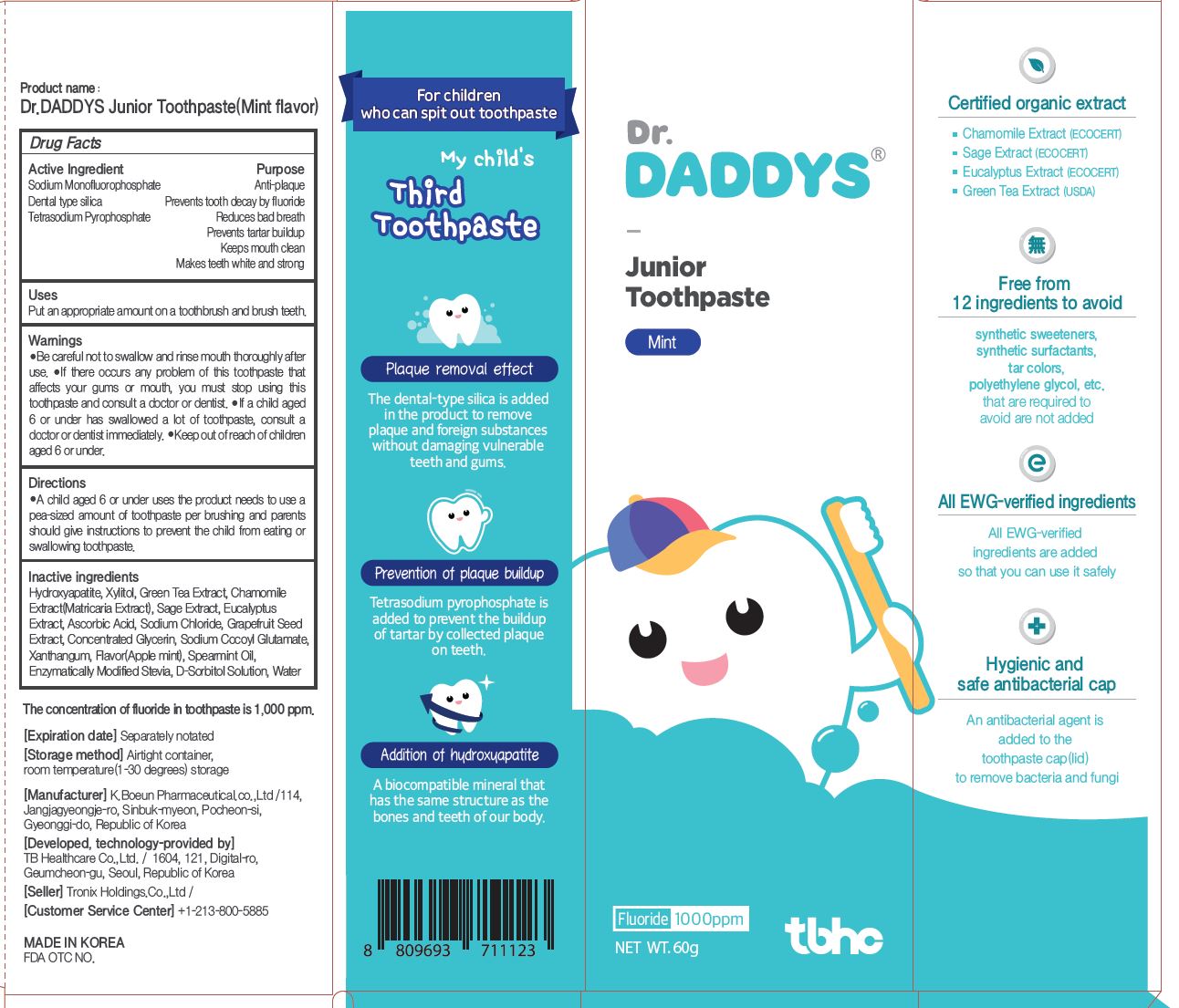 DRUG LABEL: Dr.DADDYS Junior Toothpaste(Mint flavor)
NDC: 76884-0007 | Form: PASTE, DENTIFRICE
Manufacturer: TB Healthcare Co., Ltd.
Category: otc | Type: HUMAN OTC DRUG LABEL
Date: 20220406

ACTIVE INGREDIENTS: SILICON DIOXIDE 15 g/100 g; SODIUM PYROPHOSPHATE 0.5 g/100 g; SODIUM MONOFLUOROPHOSPHATE 0.758 g/100 g
INACTIVE INGREDIENTS: XYLITOL; WATER

ACTIVE INGREDIENT

Sodium Monofluorophosphate, Dental type silica,
Tetrasodium Pyrophosphate

INACTIVE INGREDIENT

D-Sorbitol Solution
Concentrated Glycerin
Xanthangum
Sodium Cocoyl Glutamate
Ascorbic Acid
Hydroxyapatite
Xylitol
Enzymatically Modified Stevia
Sodium Chloride
Flavor(Apple mint)
Spearmint Oil
Grapefruit Seed Extract
Green Tea Extract
Matricaria Extract
Sage Extract
Eucalyptus Extract
Water

PURPOSE

Reduces bad breath, Prevents tartar buildup, Keeps mouth clean, Makes teeth white and strong, Prevent periodontal disease, gum disease

Keep out of reach of children

INDICATIONS AND USAGE

Put an appropriate amount on a toothbrush and brush teeth

WARNINGS

1. Be careful not to swallow. Rinse mouth thoroughly after use

2. If the use of toothpaste causes abnormalities such as gums or mouth injury, discontinue use and consult a doctor or dentist.

3. For children under 6 years of age, use a small amount of toothpaste as small as pea per use, and use under the guidance of a guardian to avoid sucking or swallowing.

4. If a child under 6 years old swallows large amount, consult with a doctor or dentist immediately.

5. Keep out of the reach of children under 6 years of age.

DOSAGE AND ADMINISTRATION

For dental use only